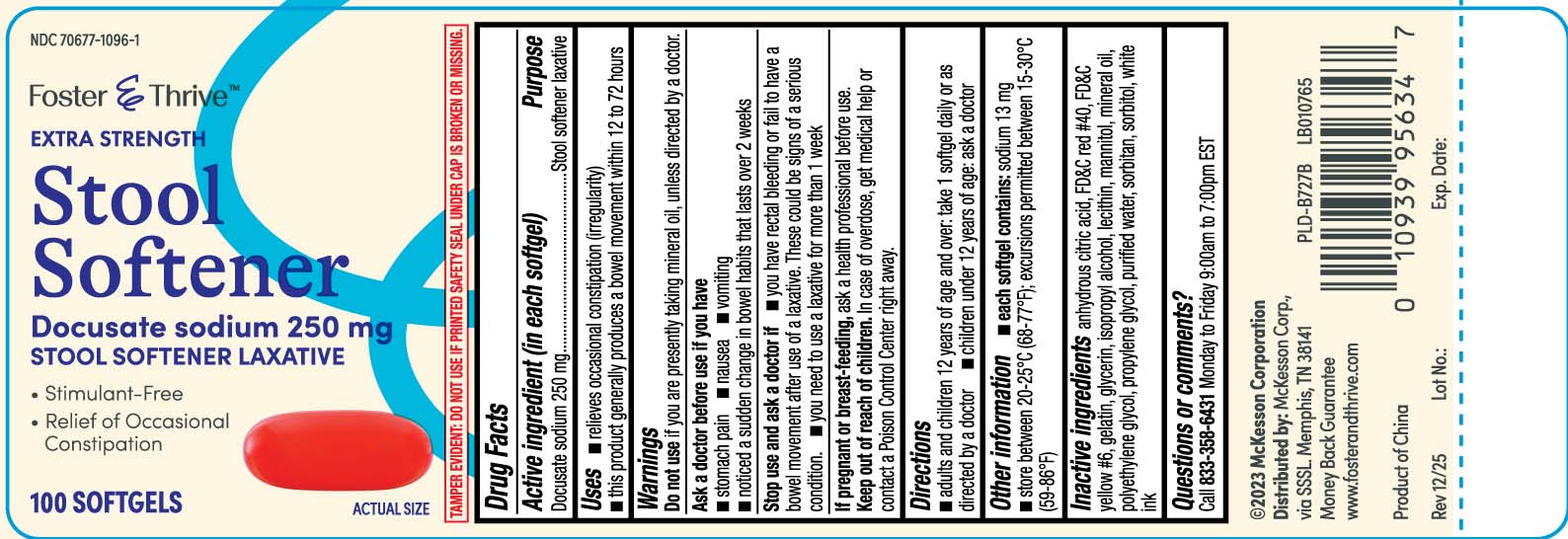 DRUG LABEL: Stool Softener
NDC: 70677-1096 | Form: CAPSULE, LIQUID FILLED
Manufacturer: Strategic Sourcing Services LLC
Category: otc | Type: HUMAN OTC DRUG LABEL
Date: 20260107

ACTIVE INGREDIENTS: DOCUSATE SODIUM 250 mg/1 1
INACTIVE INGREDIENTS: FD&C RED NO. 40; FD&C YELLOW NO. 6; GELATIN; GLYCERIN; POLYETHYLENE GLYCOL, UNSPECIFIED; PROPYLENE GLYCOL; WATER; SORBITOL; ANHYDROUS CITRIC ACID; ISOPROPYL ALCOHOL; LECITHIN, SOYBEAN; MANNITOL; MINERAL OIL; SORBITAN

Drug Facts

Active ingredient (in each softgel)

Docusate sodium 250 mg

Purpose

Stool softener laxative

Uses

- relieves occasional constipation (irregularity)
- this product generally produces a bowel movement within 12 to 72 hours

Warnings

Do not use

if you are presently taking mineral oil, unless directed by a doctor.

Ask a doctor before use if you have

- stomach pain
- nausea
- vomiting
- noticed a sudden change in bowel habits that last over 2 weeks

Stop use and ask a doctor if

- you have rectal bleeding or fail to have a bowel movement after use of a laxative. These could be signs of a serious condition.
- you need to use a laxative for more than 1 week

If pregnant or breast-feeding

ask a health professional before use.

Keep out of reach of children.

In case of overdose, get medical help or contact a Poison Control Center right away.

Directions

- adults and children 12 years of age and over: take 1 softgel daily or as directed by a doctor
- children under 12 years of age: ask a doctor

Other information

- each softgel contains: sodium 13 mg
- store between 20-25ºC(68-77ºF); excursions permitted between 15-30ºC (59-86ºF)

Inactive Ingredients

anhydrous citric acid, FD&C red #40, FD&C yellow #6, gelatin, glycerin, isopropyl alcohol, lecithin, mannitol, mineral oil, polyethylene glycol, propylene glycol, purified water, sorbitan, sorbitol, white ink

Questions or comments?

Call 1-833-358-6431 Monday to Friday 9:00am to 7:00pm EST

Principal Display Panel

EXTRA STRENGTH

Stool Softener

Docusate Sodium 250 mg

STOOL SOFTENER LAXATIVE

- Stimulant-free
- Relief of Occasional Constipation

SOFTGELS

TAMPER EVIDENT: DO NOT USE IF PRINTED SAFETY SEAL UNDER CAP IS BROKEN OR MISSING.

Distributed by: McKesson Corp.,

via SSSL Memphis, TN 38141

www.fosterandthrive.com

Product Label

Foster and Thrive Stool Softener